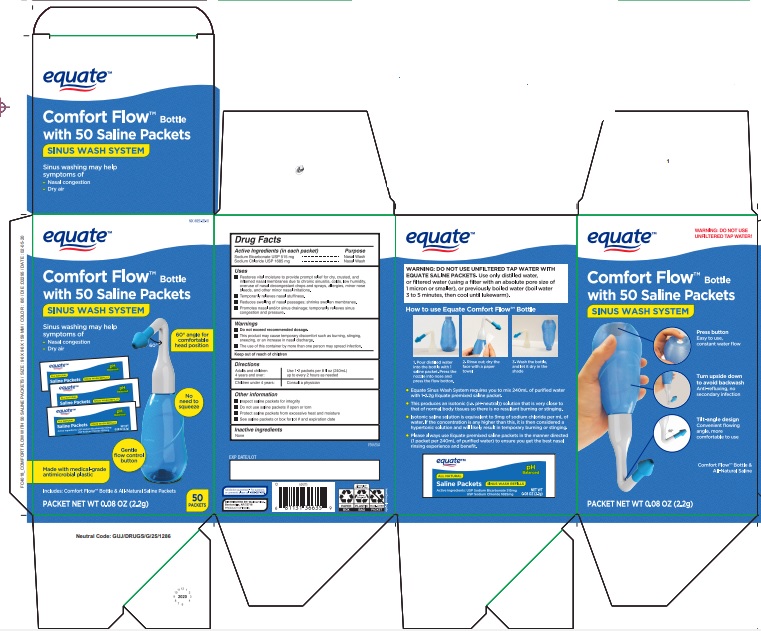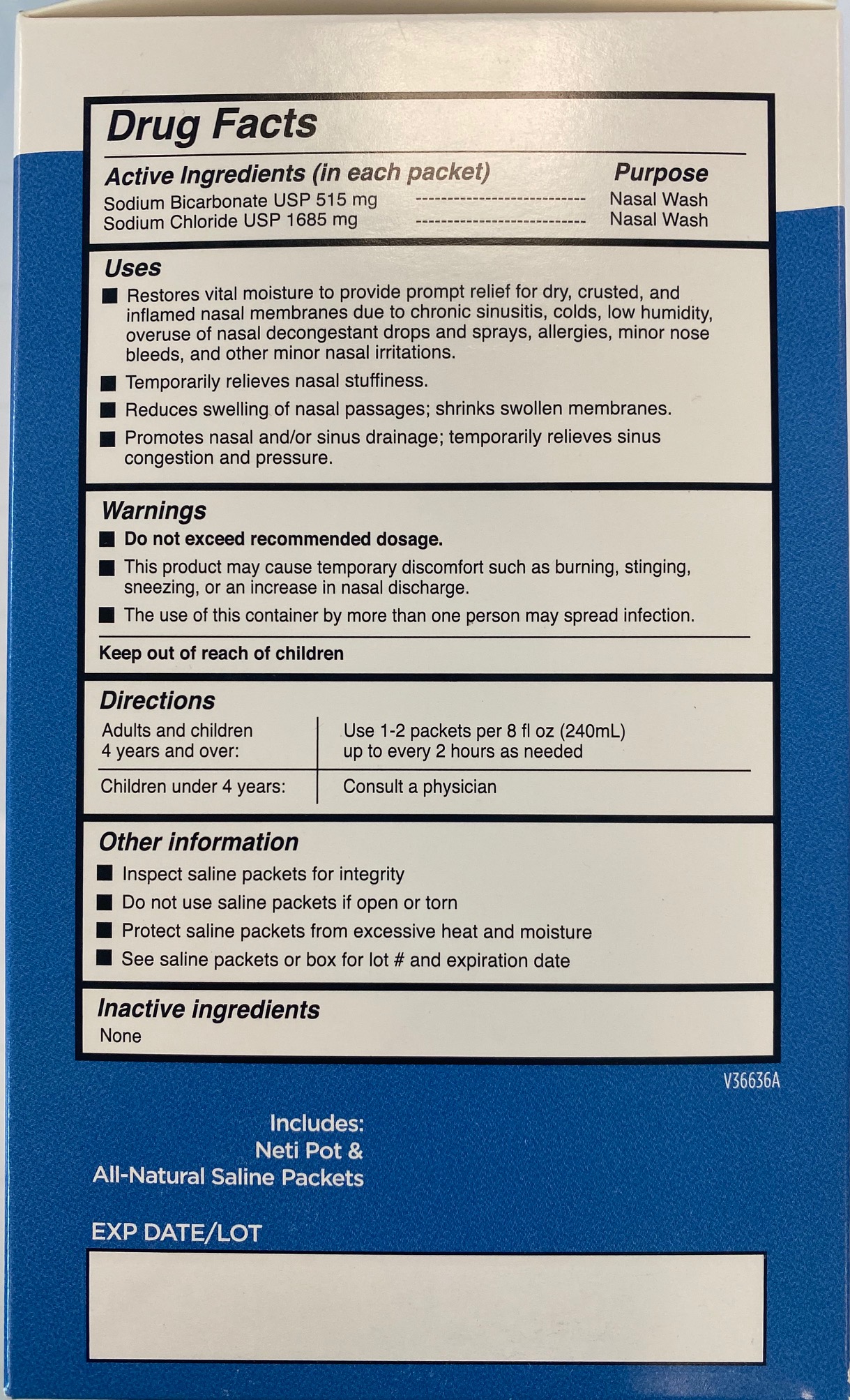 DRUG LABEL: Equate Comfort Flow Sinus wash
NDC: 49035-539 | Form: POWDER, FOR SOLUTION
Manufacturer: WALMART INC
Category: otc | Type: HUMAN OTC DRUG LABEL
Date: 20260119

ACTIVE INGREDIENTS: SODIUM BICARBONATE 0.515 g/2.2 g; SODIUM CHLORIDE 1.685 g/2.2 g
INACTIVE INGREDIENTS: WATER

Comfort Flow Nasal Wash

Active Ingredients

Sodium Bicarbonate USP 515 mg

Sodium Chloride USP 1685 mg

Purpose

Nasal Wash

Uses

- Restores vital moisture to provide prompt relief for dry , crusted and inflamed nasal membranes due to chronic sinusitis, colds, low humidity, overuse of nasal decongestant drops and sprays, allergies, minor nose bleeds and other minor nasal irritations.
- Temporarily relieves nasal stuffiness.
- Reduces swelling of nasal passages; shrinks swollen membranes.
- Promotes nasal and/or sinus drainage; temporarily relieves sinus congestion and pressure.

Warnings

- Do not exceed recommended dosage.
- This product may cause temporary discomfort such as burning, stinging, sneezing or an increase in nasal discharge.
- The use of this container by more than one person may spread infection.

Keep out of reach of children

Directions

- Adults and children 4 years and over : Use 1-2 packets per 240 ml up to every 2 hours as needed
- Children under 4 years : Consult a physician

Other Information

- Inspect saline packets for integrity
- Do not use saline packets if open or torn
- Protect saline packets from excessive heat and moisture
- See saline packets or box for lot# and expiration date

Inactive Ingredients

None